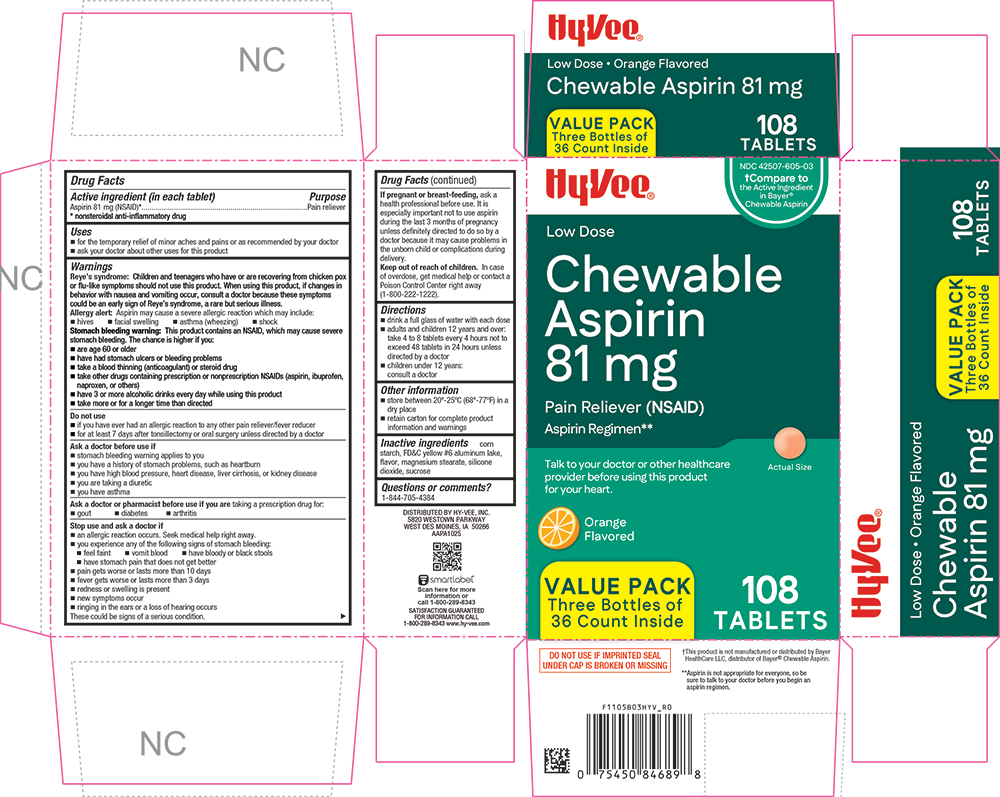 DRUG LABEL: Chewable Aspirin 81 mg
NDC: 42507-605 | Form: TABLET, CHEWABLE
Manufacturer: HYVEE INC
Category: otc | Type: HUMAN OTC DRUG LABEL
Date: 20260113

ACTIVE INGREDIENTS: ASPIRIN 81 mg/1 1
INACTIVE INGREDIENTS: STARCH, CORN; FD&C YELLOW NO. 6; MAGNESIUM STEARATE; SILICON DIOXIDE; SUCROSE

1105B-2026-0113

Drug Facts

Active ingredient (in each tablet)

Aspirin 81 mg (NSAID)*

* nonsteroidal anti-inflammatory drug

Purpose

Pain reliever

Uses

- for the temporary relief of minor aches and pains or as recommended by your doctor
- ask your doctor about other uses for this product

Warnings

Reye's syndrome

Children and teenagers who have or are recovering from chicken pox or flu-like symptoms should not use this product. When using this product, if changes in behavior with nausea and vomiting occur, consult a doctor because these symptoms could be an early sign of Reye’s syndrome, a rare but serious illness.

Allergy alert

Aspirin may cause a severe allergic reaction which may include:

- hives
- facial swelling
- asthma (wheezing)
- shock

Stomach bleeding warning

This product contains an NSAID, which may cause severe stomach bleeding. The chance is higher if you:

- are age 60 or older
- have had stomach ulcers or bleeding problems
- take a blood thinning (anticoagulant) or steroid drug
- take other drugs containing prescription or nonprescription NSAIDs (aspirin, ibuprofen, naproxen, or others)
- have 3 or more alcoholic drinks every day while using this product
- take more or for a longer time than directed

Do not use

- if you have ever had an allergic reaction to any other pain reliever/fever reducer
- for at least 7 days after tonsillectomy or oral surgery unless directed by a doctor

Ask a doctor before use if

- stomach bleeding warning applies to you
- you have a history of stomach problems, such as heartburn
- you have high blood pressure, heart disease, liver cirrhosis, or kidney disease
- you are taking a diuretic
- you have asthma

Ask a doctor or pharmacist before use if you aretaking a prescription drug for:

- gout
- diabetes
- arthritis

Stop use and ask a doctor if

- an allergic reaction occurs. Seek medical help right away.
- you experience any of the following signs of stomach bleeding:
  - feel faint
  - vomit blood
  - have bloody or black stools
  - have stomach pain that does not get better
- pain gets worse or lasts more than 10 days
- fever gets worse or lasts more than 3 days
- redness or swelling is present
- new symptoms occur
- ringing in the ears or a loss of hearing occurs

These could be signs of a serious condition.

PREGNANCY OR BREAST FEEDING

If pregnant or breast-feeding,ask a health professional before use. It is especially important not to use aspirin during the last 3 months of pregnancy unless definitely directed to do so by a doctor because it may cause problems in the unborn child or complications during delivery.

Keep out of reach of children.In case of overdose, get medical help or contact a Poison Control Center right away (1-800-222-1222).

Directions

- drink a full glass of water with each dose
- adults and children 12 years and over: take 4 to 8 tablets every 4 hours not to exceed 48 tablets in 24 hours unless directed by a doctor
- children under 12 years: consult a doctor

Other information

- store between 20°-25°C (68°-77°F) in a dry place
- retain carton for complete product information and warnings

Inactive ingredients

corn starch, FD&C yellow #6 aluminum lake, flavor, magnesium stearate, silicon dioxide, sucrose

Questions or comments?

1-844-705-4384

PRINCIPAL DISPLAY PANEL

HyVee®

NDC 42507-605-03

†Compare to the Active Ingredient in Bayer® Chewable Aspirin

Low Dose

Chewable Aspirin 81 mg

Pain Reliever (NSAID)

Aspirin Regimen**

Talk to your doctor or other healthcare provider before using this product for your heart.

Actual Size

Orange Flavored

VALUE PACK

Three Bottles of 36 County Inside

108 TABLETS